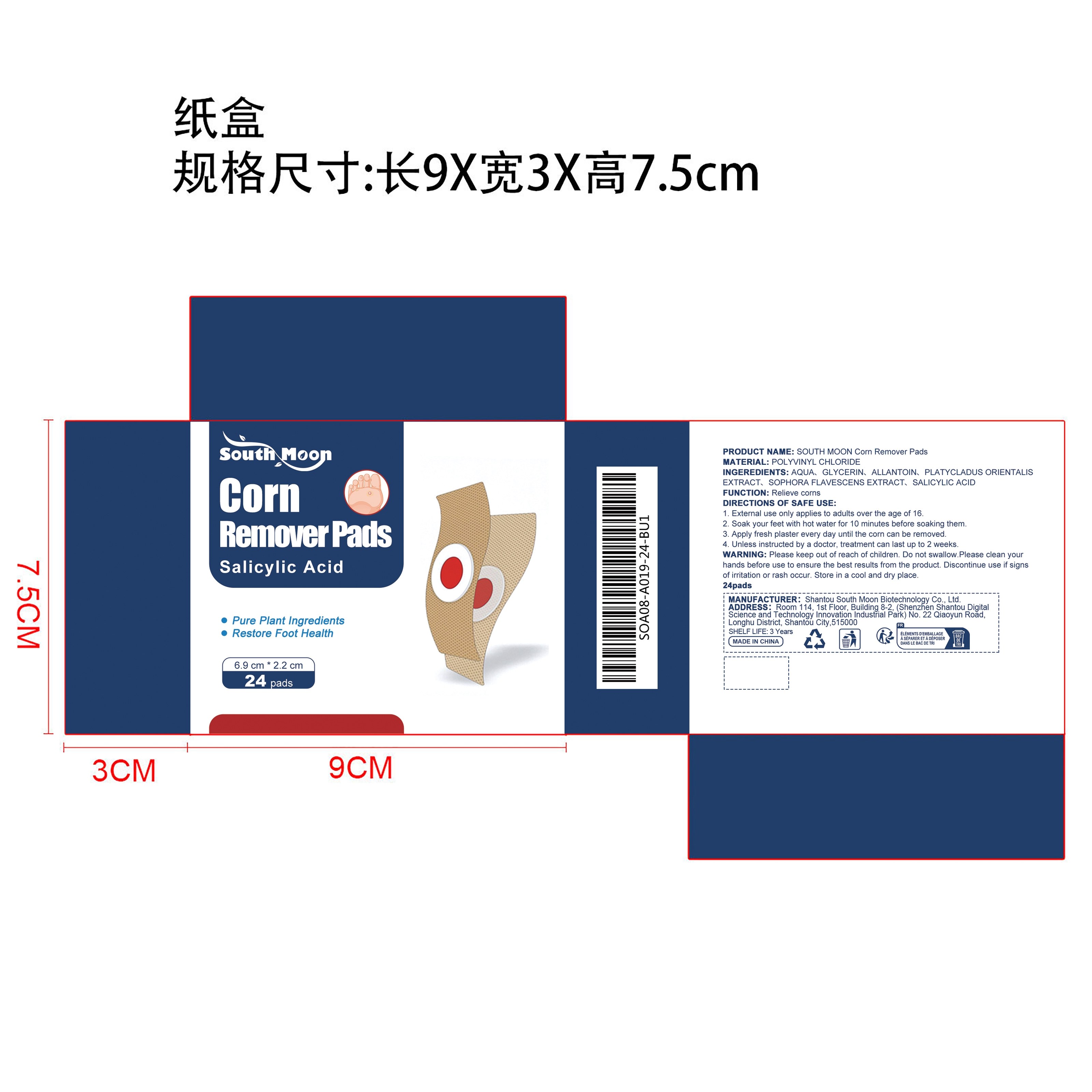 DRUG LABEL: SOUTH MOON Corn Remover Pads
NDC: 84983-019 | Form: PATCH
Manufacturer: Shantou South Moon Biotechnology Co., Ltd.
Category: otc | Type: HUMAN OTC DRUG LABEL
Date: 20251215

ACTIVE INGREDIENTS: PLATYCLADUS ORIENTALIS LEAF 0.0096 mg/48 mg; SOPHORA FLAVESCENS ROOT 0.0096 mg/48 mg
INACTIVE INGREDIENTS: ALLANTOIN 0.048 mg/48 mg; SALICYLIC ACID 0.0096 mg/48 mg; GLYCERIN 0.48 mg/48 mg; AQUA 47.4432 mg/48 mg

ACTIVE INGREDIENT

PLATYCLADUS ORIENTALIS EXTRACT、SOPHORA FLAVESCENS EXTRACT

PURPOSE

Relieve corns

WHEN USING

1. External use only applies to adults over the age of 16.

2. Soak your feet with hot water for 10 minutes before soaking them.

3. Apply fresh plaster every day until the corn can be removed.

4. Unless instructed by a doctor, treatment can last up to 2 weeks.

WARNINGS

Please keep out of reach of children. Do not swallow.Please clean your hands before use to ensure the best results from the product. Discontinue use if signs of irritation or rash occur. Store in a cool and dry place.

DO NOT USE

Discontinue use if signs of irritation or rash occur.

STOP USE

Discontinue use if signs of irritation or rash occur.

KEEP OUT OF REACH OF CHILDREN

Please keep out of reach of children. Do not swallow.

STORAGE AND HANDLING

Store in a cool and dry place.

INACTIVE INGREDIENT

AQUA、GLYCERIN、ALLANTOIN、SALICYLIC ACID

DOSAGE AND ADMINISTRATION

1. External use only applies to adults over the age of 16.

2. Soak your feet with hot water for 10 minutes before soaking them.

3. Apply fresh plaster every day until the corn can be removed.

4. Unless instructed by a doctor, treatment can last up to 2 weeks.

INDICATIONS AND USAGE

1. External use only applies to adults over the age of 16.

2. Soak your feet with hot water for 10 minutes before soaking them.

3. Apply fresh plaster every day until the corn can be removed.

4. Unless instructed by a doctor, treatment can last up to 2 weeks.